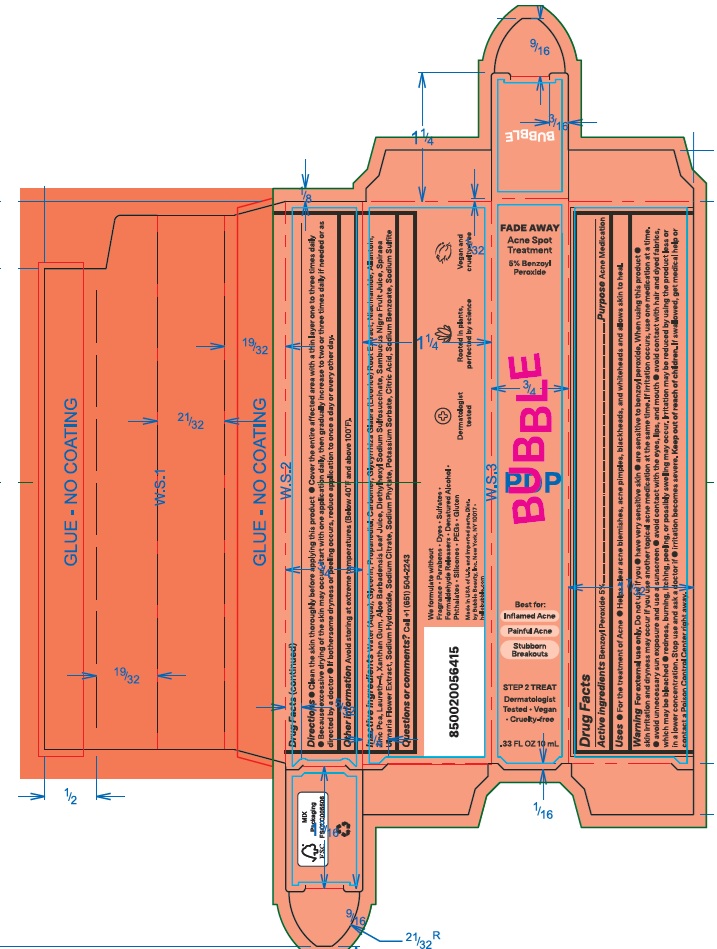 DRUG LABEL: Bubble Fade Away Acne Spot Treatment
NDC: 83509-003 | Form: EMULSION
Manufacturer: BUBBLE BEAUTY
Category: otc | Type: HUMAN OTC DRUG LABEL
Date: 20250120

ACTIVE INGREDIENTS: BENZOYL PEROXIDE 50 mg/1 mL
INACTIVE INGREDIENTS: SODIUM PHYTATE; POTASSIUM SORBATE; SODIUM BENZOATE; GLYCYRRHIZA GLABRA (LICORICE) ROOT; NIACINAMIDE; ALLANTOIN; ZINC PCA; LAURETH-4; XANTHAN GUM; DIETHYLHEXYL SODIUM SULFOSUCCINATE; ALOE VERA LEAF; SAMBUCUS NIGRA FRUIT JUICE; FILIPENDULA ULMARIA FLOWER; CITRIC ACID MONOHYDRATE; SODIUM HYDROXIDE; WATER; CARBOMER; GLYCERIN; PROPANEDIOL; SODIUM SULFITE; SODIUM CITRATE, UNSPECIFIED FORM

Bubble Fade Away Acne Spot Treatment

Active ingredients

Benzoyl Peroxide 5%

Purpose

Acne Medication

Uses

- For the treatment of acne
- Helps clear acne blemishes, acne pimples, blackheads, and whiteheads and allows skin to heal.

Warnings

For external use only.

Do not use if you

- have very sensitive skin
- are sensitive to benzoyl peroxide

When using this product

- skin irritation or dryness may occur if you use another topical acne medication at the same time. If irritation occurs, use one medication at a time
- avoid unnecessary sun exposure and use a sunscreen
- avoid contact with the eyes, lips, and mouth
- avoid contact with hair and dyed fabrics, which may be bleached
- redness, burning, itching, peeling, or possibly swelling may occur. Irritation may be reduced by using the product less or in a lower concentration.

Stop use and ask a doctor if

- irritation becomes severe.

Keep out of reach of children.

If swallowed, get medical help or contact a Poison Control Center right away.

Directions

- Clean the skin thoroughly before applying this product.
- Cover the entire affected area with a thin layer one to three times daily.
- Because excessive drying of the skin may occur, start with one application daily, then gradually increase to two or three times daily if needed or as directed by a doctor.
- If bothersome dryness or peeling occurs, reduce application to once a day or every other day.

Other information

- Avoid storing at extreme temperatures (Below 40F and above 100F).

Inactive ingredients

Water (Aqua), Glycerin, Propanediol, Carbomer, Glycyrrhiza Glabra (Licorice) Root Extract, Niacinamide, Allantoin, Zinc Pca, Laureth-4, Xanthan Gum, Aloe Barbadensis Leaf Juice, Diethylhexyl Sodium Sulfosuccinate, Sambucus Nigra Fruit Juice, Spiraea Ulmaria Flower Extract, Sodium Hydroxide, Sodium Citrate, Sodium Phytate, Potassium Sorbate, Citric Acid, Sodium Benzoate, Sodium Sulfite

Questions or comments?

Call +1 (651) 504-2243